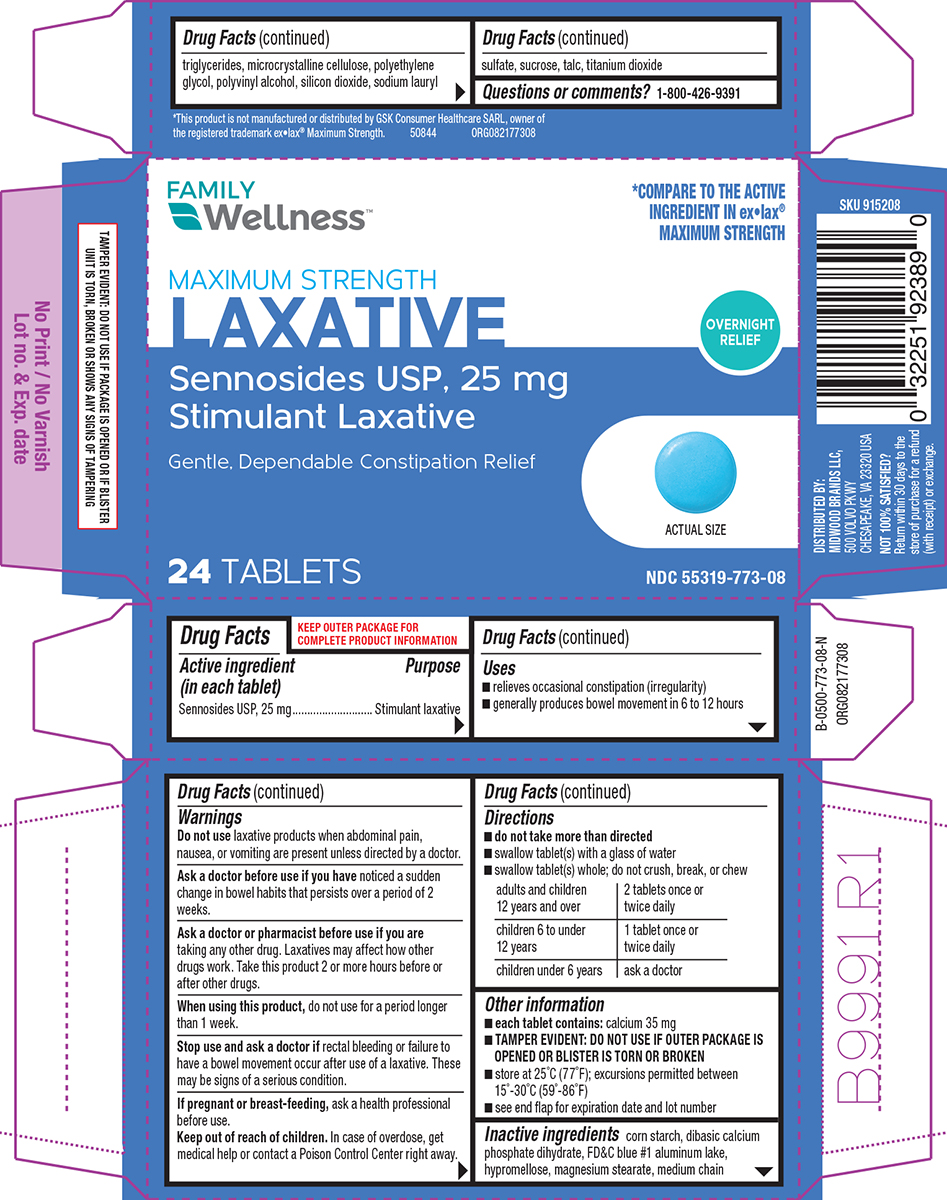 DRUG LABEL: Laxative
NDC: 55319-773 | Form: TABLET, FILM COATED
Manufacturer: Family Dollar Services Inc
Category: otc | Type: HUMAN OTC DRUG LABEL
Date: 20260202

ACTIVE INGREDIENTS: SENNOSIDES 25 mg/1 1
INACTIVE INGREDIENTS: STARCH, CORN; DIBASIC CALCIUM PHOSPHATE DIHYDRATE; FD&C BLUE NO. 1 ALUMINUM LAKE; HYPROMELLOSE, UNSPECIFIED; MAGNESIUM STEARATE; MEDIUM-CHAIN TRIGLYCERIDES; MICROCRYSTALLINE CELLULOSE; POLYETHYLENE GLYCOL, UNSPECIFIED; POLYVINYL ALCOHOL, UNSPECIFIED; SILICON DIOXIDE; SODIUM LAURYL SULFATE; SUCROSE; TALC; TITANIUM DIOXIDE

Family Wellness 44-773

Active ingredient (in each tablet)

Sennosides USP, 25 mg

Purpose

Stimulant laxative

Uses

- relieves occasional constipation (irregularity)
- generally produces bowel movement in 6 to 12 hours

Warnings

Do not use

laxative products when abdominal pain, nausea, or vomiting are present unless directed by a doctor

Ask a doctor before use if you have

noticed a sudden change in bowel habits that persists over a period of 2 weeks.

Ask a doctor or pharmacist before use if you are

taking any other drug. Laxatives may affect how other drugs work. Take this product 2 or more hours before or after other drugs.

When using this product,

do not use for a period longer than 1 week.

Stop use and ask a doctor if

rectal bleeding or failure to have a bowel movement occur after use of a laxative. These may be signs of a serious condition.

If pregnant or breast-feeding,

ask a health professional before use.

Keep out of reach of children.

In case of overdose, get medical help or contact a Poison Control Center right away.

Directions

- do not take more than directed
- swallow tablet(s) with a glass of water
- swallow tablet(s) whole; do not crush, break, or chew

adults and children 12 years and over | 2 tablets once or twice daily
children 6 to under 12 years | 1 tablet once or twice daily
children under 6 years | ask a doctor

Other information

- each tablet contains: calcium 35 mg
- TAMPER EVIDENT: DO NOT USE IF OUTER PACKAGE IS OPENED OR BLISTER IS TORN OR BROKEN
- store at 25°C (77°F); excursions permitted between 15°-30°C (59°-86°F)
- see end flap for expiration date and lot number

Inactive ingredients

corn starch, dibasic calcium phosphate dihydrate, FD&C blue #1 aluminum lake, hypromellose, magnesium stearate, medium chain triglycerides, microcrystalline cellulose, polyethylene glycol, polyvinyl alcohol, silicon dioxide, sodium lauryl sulfate, sucrose, talc, titanium dioxide

Questions or comments?

1-800-426-9391

Principal display panel

FAMILY
Wellness™

*COMPARE TO THE ACTIVE
INGREDIENT IN ex•lax®
MAXIMUM STRENGTH

MAXIMUM STRENGTH
LAXATIVE
Sennosides USP, 25 mg
Stimulant Laxative

Gentle, Dependable Constipation Relief

24 TABLETS

OVERNIGHT
RELIEF

ACTUAL SIZE

NDC 55319-773-08

TAMPER EVIDENT: DO NOT USE IF PACKAGE IS OPENED OR IF BLISTER
UNIT IS TORN, BROKEN OR SHOWS ANY SIGNS OF TAMPERING

*This product is not manufactured or distributed by GSK Consumer Healthcare SARL, owner of
the registered trademark ex•lax® Maximum Strength. 50844 ORG082177308

DISTRIBUTED BY:
MIDWOOD BRANDS LLC,
500 VOLVO PKWY
CHESAPEAKE, VA 23320 USA

NOT 100% SATISFIED?
Return within 30 days to the
store of purchase for a refund
(with receipt) or exchange.

Family Wellness 44-773